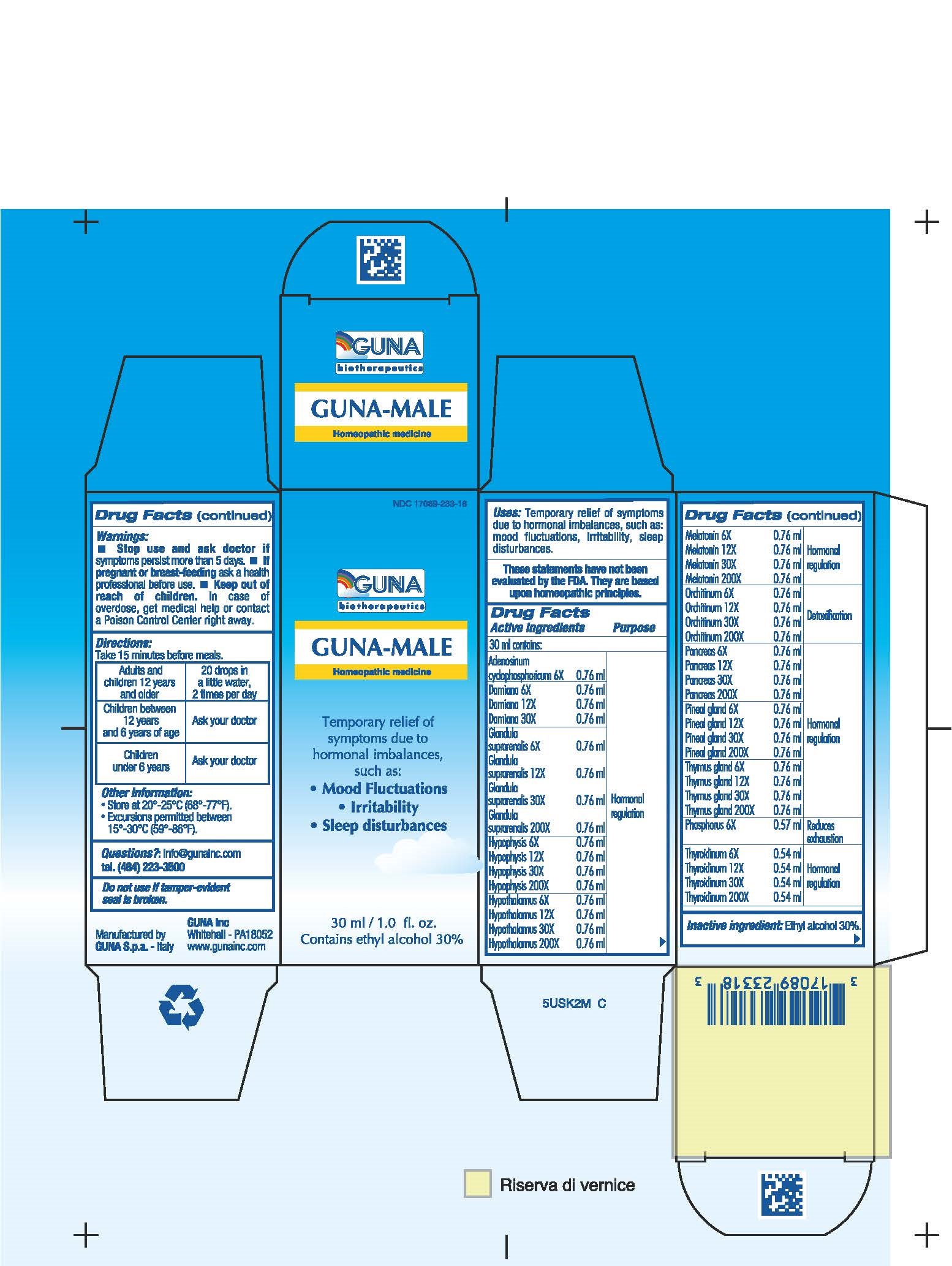 DRUG LABEL: GUNA-MALE
NDC: 17089-233 | Form: SOLUTION/ DROPS
Manufacturer: Guna spa
Category: homeopathic | Type: HUMAN OTC DRUG LABEL
Date: 20181221

ACTIVE INGREDIENTS: ADENOSINE CYCLIC PHOSPHATE 6 [hp_X]/30 mL; TURNERA DIFFUSA LEAFY TWIG 6 [hp_X]/30 mL; SUS SCROFA ADRENAL GLAND 30 [hp_X]/30 mL; SUS SCROFA PITUITARY GLAND 30 [hp_X]/30 mL; SUS SCROFA HYPOTHALAMUS 30 [hp_X]/30 mL; MELATONIN 30 [hp_X]/30 mL; SUS SCROFA TESTICLE 30 [hp_X]/30 mL; SUS SCROFA PANCREAS 30 [hp_X]/30 mL; PHOSPHORUS 6 [hp_X]/30 mL; SUS SCROFA PINEAL GLAND 30 [hp_X]/30 mL; SUS SCROFA THYMUS 30 [hp_X]/30 mL; THYROID 30 [hp_X]/30 mL
INACTIVE INGREDIENTS: ALCOHOL 9 mL/30 mL

GUNA-MALE

ACTIVE INGREDIENTS/PURPOSE

ADENOSINUM CYCLOPHOSPHORICUM 6X HORMONAL REGULATION
DAMIANA 6X 12X 30X HORMONAL REGULATION
GLANDULA SUPRARENALIS 6X 12X 30X 200X HORMONAL REGULATION
HYPOPHYSIS 6X 12X 30X 200X HORMONAL REGULATION
HYPOTHALAMUS 6X 12X 30X 200X HORMONAL REGULATION
MELATONIN 6X 12X 30X 200X HORMONAL REGULATION
ORCHITINUM 6X 12X 30X 200X DETOXIFICATION
PANCREAS 6X, 12X, 30X, 200X HORMONAL REGULATION
PHOSPHORUS 6X REDUCES EXHAUSTION
PINEAL GLAND 6X 12X 30X 200X HORMONAL REGULATION
THYMUS GLAND 6X 12X 30X 200X HORMONAL REGULATION
THYROIDINUM 6X 12X 30X 200X HORMONAL REGULATION

USES

Temporary relief of symptoms due to hormonal imbalances, such as:

- Mood Fluctuations
- Irritability
- Sleep disturbance

WARNINGS

Stop use and ask doctor if symptoms persist more than 5 days.
If pregnant or breast-feeding ask a health professional before use.
Keep out of reach of children. In case of overdose, get medical help or contact a Poison Control Center right away.
Contains ethyl alcohol 30%

PREGNANCY

If pregnant or breast-feeding ask a doctor before use

WARNINGS

Keep out of reach of children

DIRECTIONS

Take 15 minutes before meals
Adults and Children 12 years and older 20 drops in a little water 2 times per day
Children between 12 years and 6 years of age Ask your doctor.
Children under 9 years Ask your doctor.

QUESTIONS

Questions?: info@gunainc.com
Tel. (484) 223-3500

INDICATIONS AND USAGE

Take 15 minutes before meals.

Inactive ingredient: Ethyl alcohol 30%.